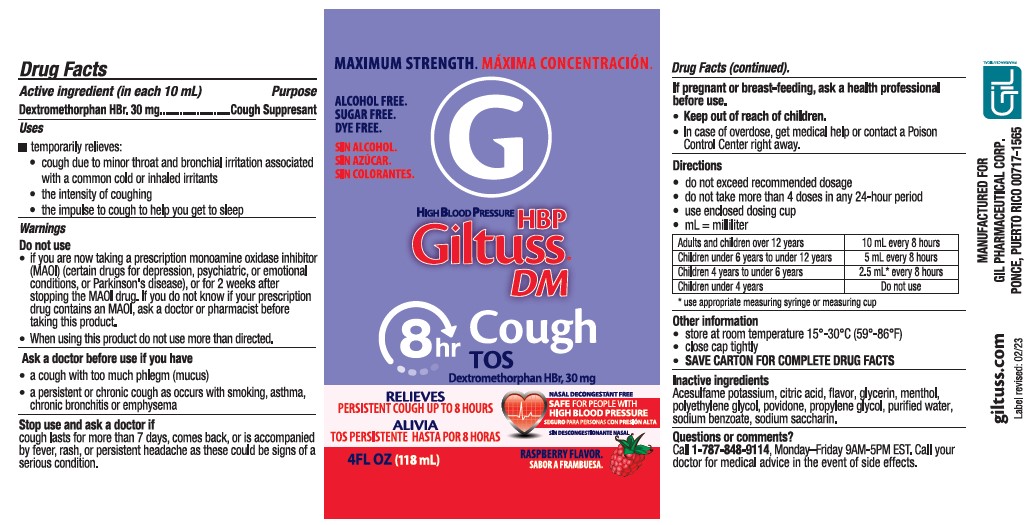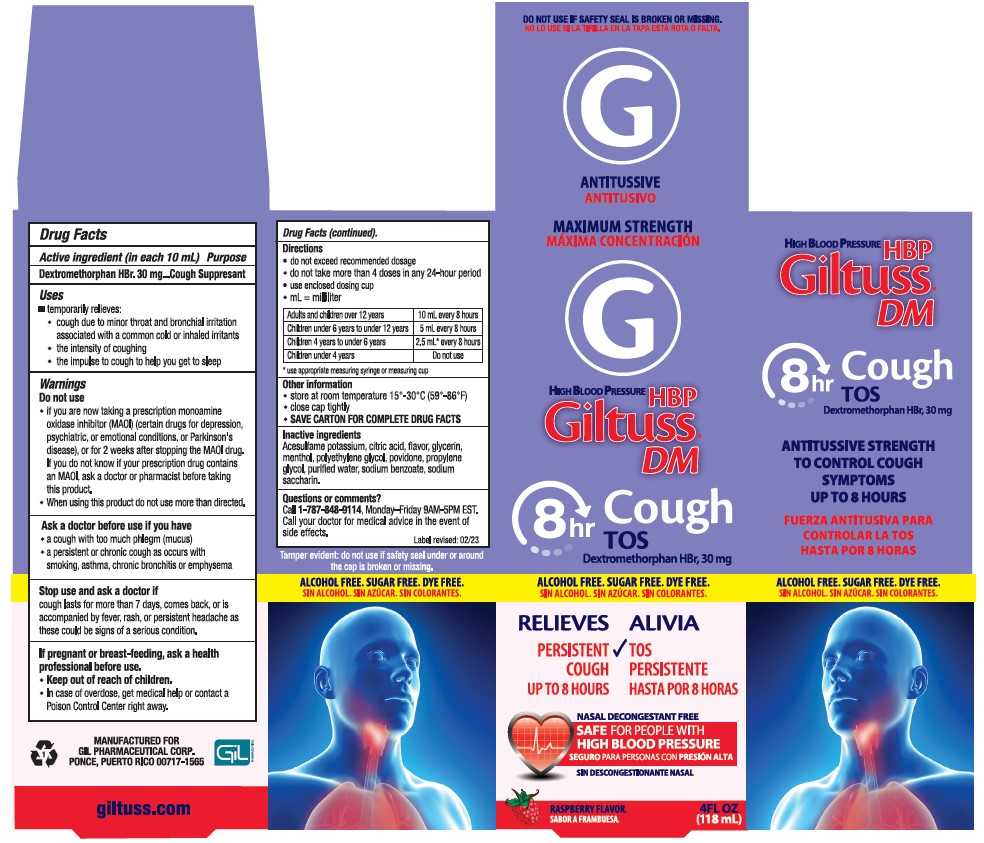 DRUG LABEL: Giltuss DM
NDC: 58552-150 | Form: SYRUP
Manufacturer: Gil Pharmaceutical Corp
Category: otc | Type: HUMAN OTC DRUG LABEL
Date: 20251009

ACTIVE INGREDIENTS: DEXTROMETHORPHAN HYDROBROMIDE 30 mg/10 mL
INACTIVE INGREDIENTS: ACESULFAME POTASSIUM; CITRIC ACID MONOHYDRATE; RASPBERRY; GLYCERIN; MENTHOL; POLYETHYLENE GLYCOL, UNSPECIFIED; POVIDONE; PROPYLENE GLYCOL; WATER; SODIUM BENZOATE; SACCHARIN SODIUM

Giltuss®DM High Blood Pressure
Dextromethorphan HBr, 30 mg
Maximum Strength

Drug Facts

Active ingredient (in each 10 mL) Purpose

Dextromethorphan HBr. 30 mg .... Cough Suppresant

Uses

■ temporarily relieves:

- cough due to minor throat and bronchial irritation associated with a common cold or inhaled irritants
- the intensity of coughing
- the impulse to cough to help you get to sleep

Warnings

Do not use

- if you are now taking a prescription monoamine oxidase inhibitor (MAOI) (certain drugs for depression, psychiatric, or emotional conditions, or Parkinson's disease), or for 2 weeks after stopping the MAOI drug. If you do not know if your prescription drug contains an MAOI, ask a doctor or pharmacist before taking this product.
- When using this product do not use more than directed.

Ask a doctor before use if you have

- a cough with too much phlegm (mucus)
- a persistent or chronic cough as occurs with smoking, asthma, chronic bronchitis or emphysema

Stop use and ask a doctor if

cough lasts for more than 7 days, comes back, or is accompanied by fever, rash, or persistent headache as these could be signs of a serious condition.

PREGNANCY OR BREAST FEEDING

If pregnant or breast-feeding, ask a health professional before use.

- Keep out of reach of children.
- In case of overdose, get medical help or contact a Poison Control Center right away.

Directions

- do not exceed recommended dosage
- do not take more than 4 doses in any 24-hour period
- use enclosed dosing cup
- ml= milliliter

Adults and children over 12 years | 10 mL every 8 hours
Children under 6 years to under 12 years | 5 mL every 8 hours
Children 4 years to under 6 years | 2.5 mL* every 8 hours
Children under 4 years | Do not use

*use appropriate measuring syringe or measuring cup

Other information

- store at room temperature 15°-30°c (59°-86°F)
- close cap tightly
- SAVE CARTON FOR COMPLETE DRUG FACTS

Inactive ingredients

Acesulfame potassium, citric acid, flavor, glycerin, menthol, polyethylene glycol, povidone, propylene glycol, purified water, sodium benzoate, sodium saccharin.

Questions or comments?

Call 1-787-848-9114, Monday-Friday 9AM-5PM EST. Call your doctor for medical advice in the event of side effects.

Label revised: 02/23

MANUFACTURED FOR
GIL PHARMACEUTICAL CORP.
PONCE, PUERTO RICO 00717-1565

PRINCIPAL DISPLAY PANEL

Giltuss DM High Blood Pressure - NDC 58552-150-04 - Bottle Label

Giltuss DM High Blood Pressure - NDC 58552-150-04 - Carton Label